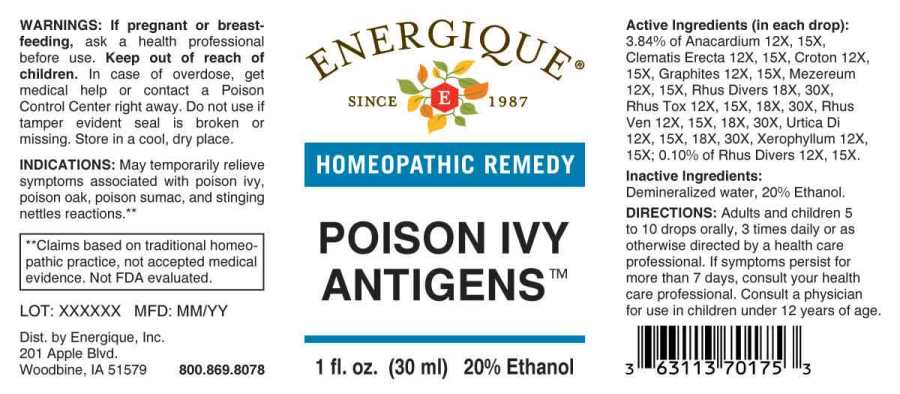 DRUG LABEL: Poison Ivy Antigens
NDC: 44911-0582 | Form: LIQUID
Manufacturer: Energique, Inc.
Category: homeopathic | Type: HUMAN OTC DRUG LABEL
Date: 20241029

ACTIVE INGREDIENTS: SEMECARPUS ANACARDIUM JUICE 12 [hp_X]/1 mL; CLEMATIS RECTA FLOWERING TOP 12 [hp_X]/1 mL; CROTON TIGLIUM SEED 12 [hp_X]/1 mL; GRAPHITE 12 [hp_X]/1 mL; DAPHNE MEZEREUM BARK 12 [hp_X]/1 mL; XEROPHYLLUM ASPHODELOIDES WHOLE 12 [hp_X]/1 mL; TOXICODENDRON DIVERSILOBUM LEAF 12 [hp_X]/1 mL; TOXICODENDRON PUBESCENS LEAF 12 [hp_X]/1 mL; TOXICODENDRON VERNIX LEAFY TWIG 12 [hp_X]/1 mL; URTICA DIOICA WHOLE 12 [hp_X]/1 mL
INACTIVE INGREDIENTS: WATER; ALCOHOL

DRUG FACTS:

ACTIVE INGREDIENTS:

(in each drop): 3.84% of Anacardium Orientale 12X, 15X, Clematis Erecta 12X, 15X, Croton Tiglium 12X, 15X, Graphites 12X, 15X, Mezereum 12X, 15, Rhus Diversiloba 18X, 30X, Rhus Tox 12X, 15X, 18X, 30X, Rhus Venenata 12X, 15X, 18X, 30X, Urtica Dioica 12X, 15X, 18X, 30X, Xerophyllum Asphodeloides 12X, 15; 0.10% of Rhus Diversiloba 12X, 15X.

INDICATIONS:

May temporarily relieve symptoms associated with poison ivy, poison oak, poison sumac, and stinging nettles reactions.**

** Claims based on traditional homeopathic practice, not accepted medical evidence. Not FDA evaluated.

WARNINGS:

If pregnant or breastfeeding, ask a health professional before use.

Keep out of reach of children. In case of overdose, get medical help or contact a Poison Control Center right away.

Do not use if tamper evident seal is broken or missing.

Store in a cool, dry place.

Keep out of reach of children. In case of overdose, get medical help or contact a Poison Control Center right away.

DIRECTIONS:

Adults and children 5 to 10 drops orally, 3 times daily or as otherwise directed by a health care professional. If symptoms persist for more than 7 days, consult your health care professional. Consult a physician for use in children under 12 years of age.

INDICATIONS:

May temporarily relieve symptoms associated with poison ivy, poison oak, poison sumac, and stinging nettles reactions.**

** Claims based on traditional homeopathic practice, not accepted medical evidence. Not FDA evaluated.

INACTIVE INGREDIENTS:

Demineralized water, 20% Ethanol.

QUESTIONS:

Dist. by Energique, Inc.
201 Apple Blvd.
Woodbine, IA 51579 800.869.8078

PACKAGE LABEL DISPLAY:

ENERGIQUE

SINCE 1987

HOMEOPATHIC REMEDY

POISON IVY

ANTIGENS

1 fl. oz. (30 ml)